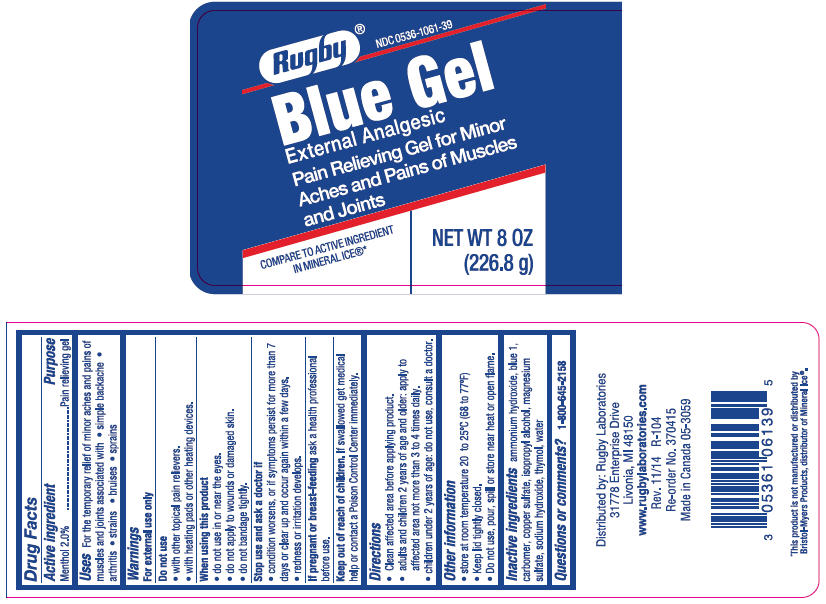 DRUG LABEL: Rugby Ice Blue
NDC: 0536-1061 | Form: GEL
Manufacturer: Rugby Laboratories
Category: otc | Type: HUMAN OTC DRUG LABEL
Date: 20240314

ACTIVE INGREDIENTS: MENTHOL, UNSPECIFIED FORM 20 mg/1 g
INACTIVE INGREDIENTS: Ammonia; FD&C Blue No. 1; CARBOXYMETHYLCELLULOSE SODIUM, UNSPECIFIED; Cupric Sulfate; Isopropyl Alcohol; Magnesium Sulfate Anhydrous; Sodium Hydroxide; Thymol; Water

Rugby® Ice Blue Gel
External Analgesic

Drug Facts

Active ingredient

Menthol 2.0%

Purpose

Pain relieving gel

Uses

For the temporary relief of minor aches and pains of muscles and joints associated with

- simple backache
- arthritis
- strains
- bruises
- sprains

Warnings

For external use only

Do not use

- with other topical pain relievers.
- with heating pads or other heating devices.

When using this product

- do not use in or near the eyes.
- do not apply to wounds or damaged skin.
- do not bandage tightly.

Stop use and ask a doctor if

- condition worsens, or if symptoms persist for more than 7 days or clear up and occur again within a few days.
- redness or irritation develops.

PREGNANCY OR BREAST FEEDING

If pregnant or breast-feeding ask a health professional before use.

Keep out of reach of children. If swallowed get medical help or contact a Poison Control Center immediately.

Directions

- Clean affected area before applying product.
- adults and children 2 years of age and older: apply to affected area not more than 3 to 4 times daily.
- children under 2 years of age: do not use, consult a doctor.

Other information

- store at room temperature 20 to 25°C (68 to 77°F)
- Keep lid tightly closed.
- Do not use, pour, spill or store near heat or open flame.

Inactive ingredients

ammonium hydroxide, blue 1, carbomer, copper sulfate, isopropyl alcohol, magnesium sulfate, sodium hydroxide, thymol, water

Questions or comments?

1-800-645-2158

Distributed by: Rugby Laboratories
31778 Enterprise Drive
Livonia, MI 48150

PRINCIPAL DISPLAY PANEL - 226.8 g Jar Label

Rugby® NDC 0536-1061-39

Blue Gel
External Analgesic
Pain Relieving Gel for Minor
Aches and Pains of Muscles
and Joints

COMPARE TO ACTIVE INGREDIENT
IN MINERAL ICE®*

NET WT 8 OZ
(226.8 g)